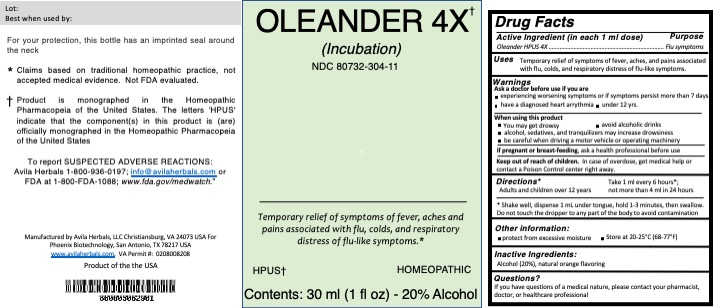 DRUG LABEL: Oleander 4X
NDC: 80732-304 | Form: TINCTURE
Manufacturer: Avila Herbals
Category: homeopathic | Type: HUMAN OTC DRUG LABEL
Date: 20220127

ACTIVE INGREDIENTS: NERIUM OLEANDER LEAF 4 [hp_X]/30 U
INACTIVE INGREDIENTS: WATER 23 U/30 U; ORANGE OIL TERPENELESS 0.9 mL/30 U; ALCOHOL 6 U/30 U

Oleander 4X

Active Ingredient (in each 1ml dose)

Oleander HPUS 4X

Purpose

Flu symptoms

Inactive Ingredients

purified water, ethanol, natural orange flavor

Uses

Temporary relief of symptoms of fever, aches and pains associated with flu, colds, and respiratory distress of flu-like symptoms.

Warnings

Ask a Doctor before use if you are:

experiencing worsening symptoms or if symptoms persist more than 7 days, have a diagnosed heart arrythmia, under 12 yrs.

When using this product

You may get drowsy

avoid alcoholic drinks

alcohol, sedatives, and tranquilizers may increase drowziness

be careful when driving a motor vehicle or operating machinery

If pregnant or breast-feeding, ask a health professional before use

Keep out of reach of chldren. In case of overdose, get medical help or contact posion Control Center right away

Other Information

protect from excessive moisture

Store at 20-25C (68-77F)

Warnings

Warnings: If symptoms worsen or persist for more than 7 days, or if pregnant or nursing or if under 12 yrs. old, consult a licensed practioner. Do not use if you are taking a cardiac glycoside for heart arrythmia. Keep out of reach of children

Dosage and Directions

Take 1ml every 6 hours; not more than 4 ml in a 24 hour period

Uses

Temporary relief of symptoms of fever, aches, and pains associated with flu, colds, and respiratory distress of flu-like symptoms.

Oleander 4X

Oleander 4X, Incubation

Temporary relief of symptoms of fever, aches and pains associated with flu, colds, and respiratory distress of flu-like symptoms.

HPUS

Homeopathic
Contents: 15 ml, 20% alcohol.